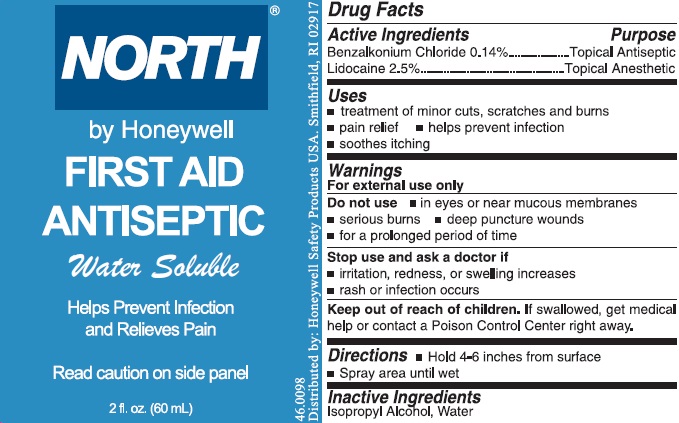 DRUG LABEL: NORTH Antiseptic First Aid
NDC: 0498-0016 | Form: SPRAY, METERED
Manufacturer: North Safety Products, LLC.
Category: otc | Type: HUMAN OTC DRUG LABEL
Date: 20140516

ACTIVE INGREDIENTS: LIDOCAINE 1912.5 mg/90 mL; BENZALKONIUM CHLORIDE 107.1 mg/90 mL
INACTIVE INGREDIENTS: ISOPROPYL ALCOHOL; WATER

NORTH Antiseptic Pump Spray

Active Ingredients

Benzalkonium Chloride 0.14%
Lidocaine 2.5%

Purpose

Topical Antiseptic
Topical Anesthetic

Uses

- treatment of minor cuts, scratches and burns
- pain relief
- helps prevent infection
- soothes itching

Warnings

For external use only

Do not use

- in eyes or near mucous membranes
- serious burns
- deep puncture wounds
- for a prolonged period of time

Stop use and ask a doctor if

- irritation, redness, or swelling increases
- rash or infection occurs

Directions

- Hold 4-6 inches from surface
- Spray area until wet

Inactive Ingredients

Isopropyl Alcohol, Water